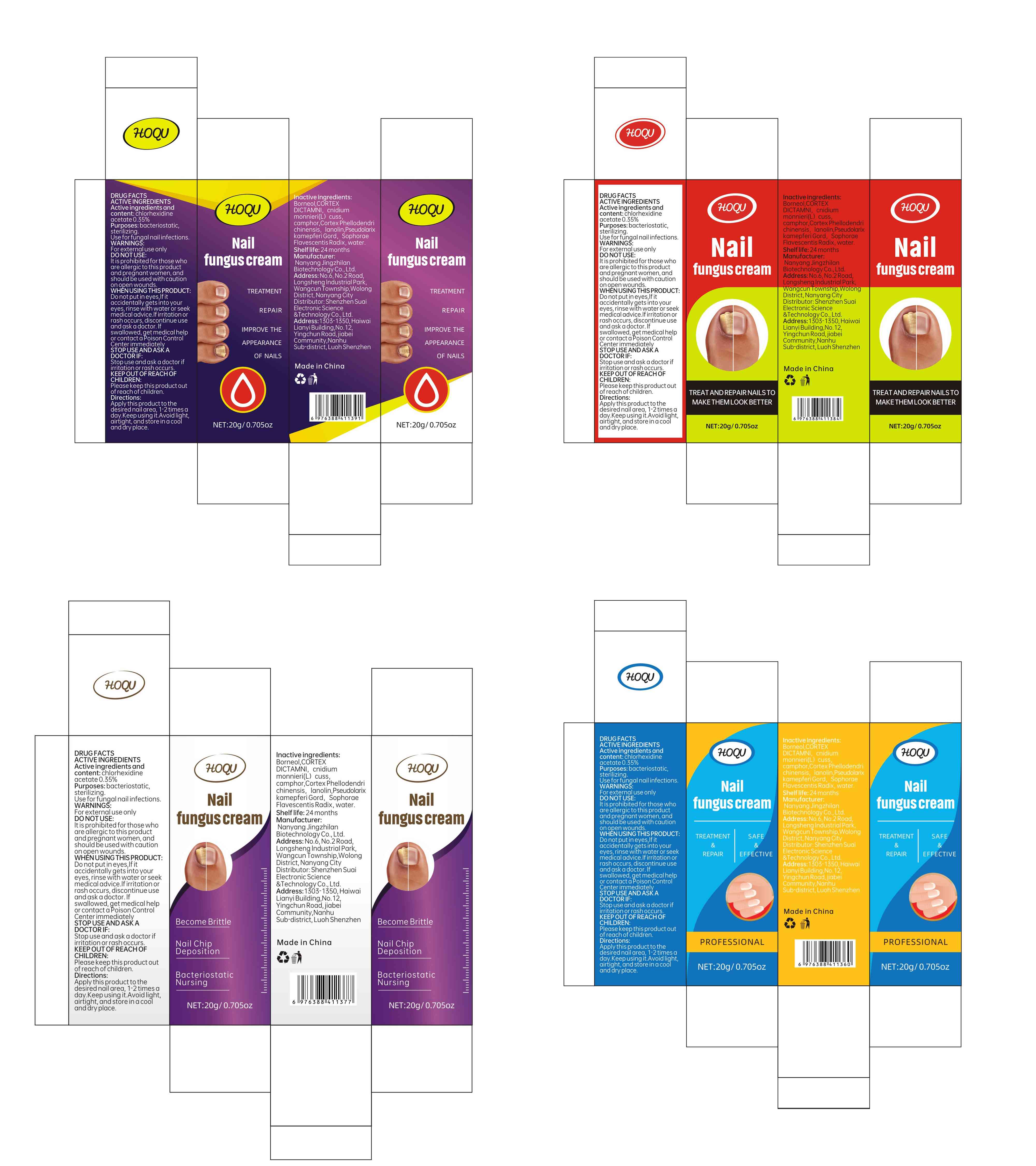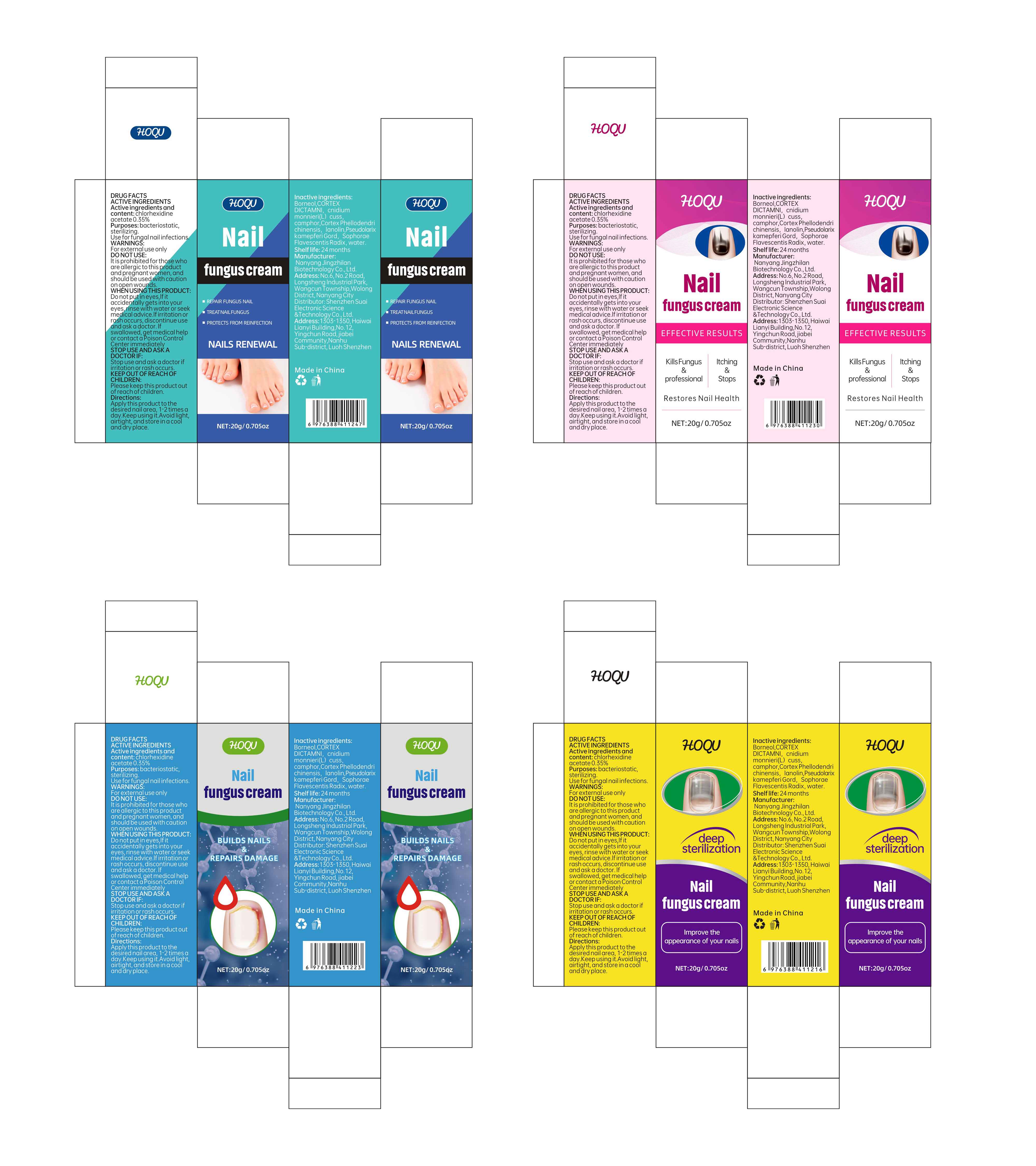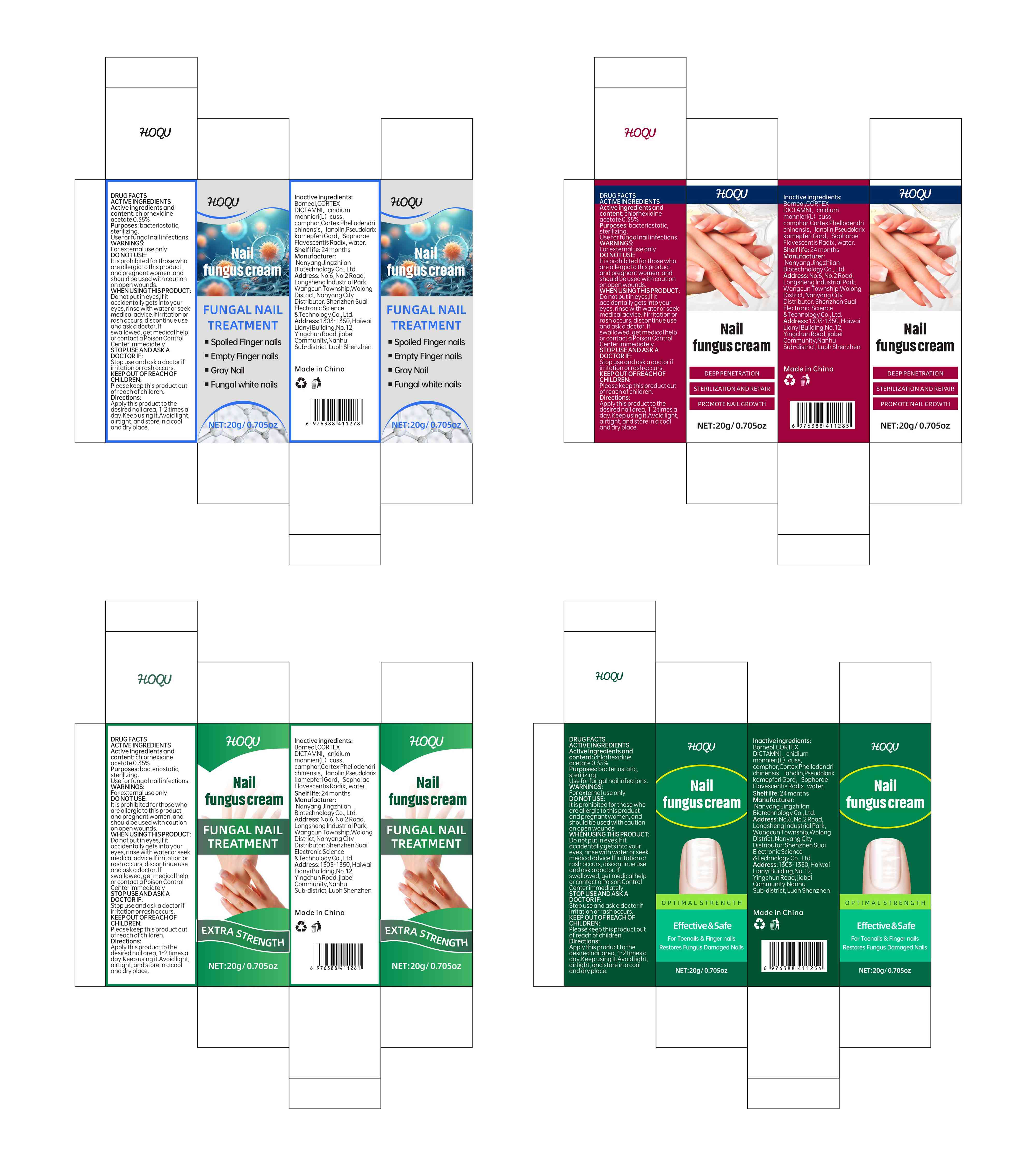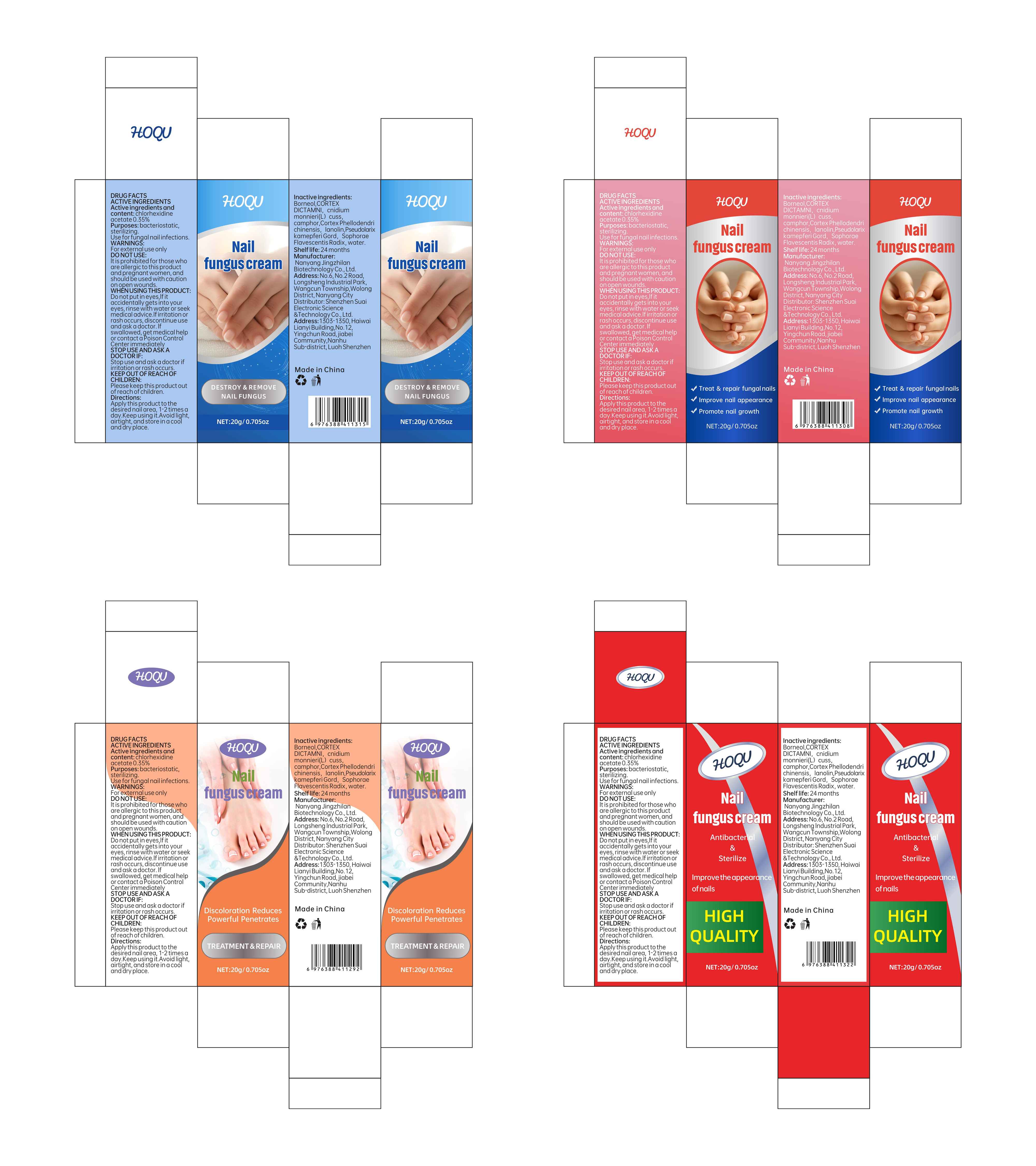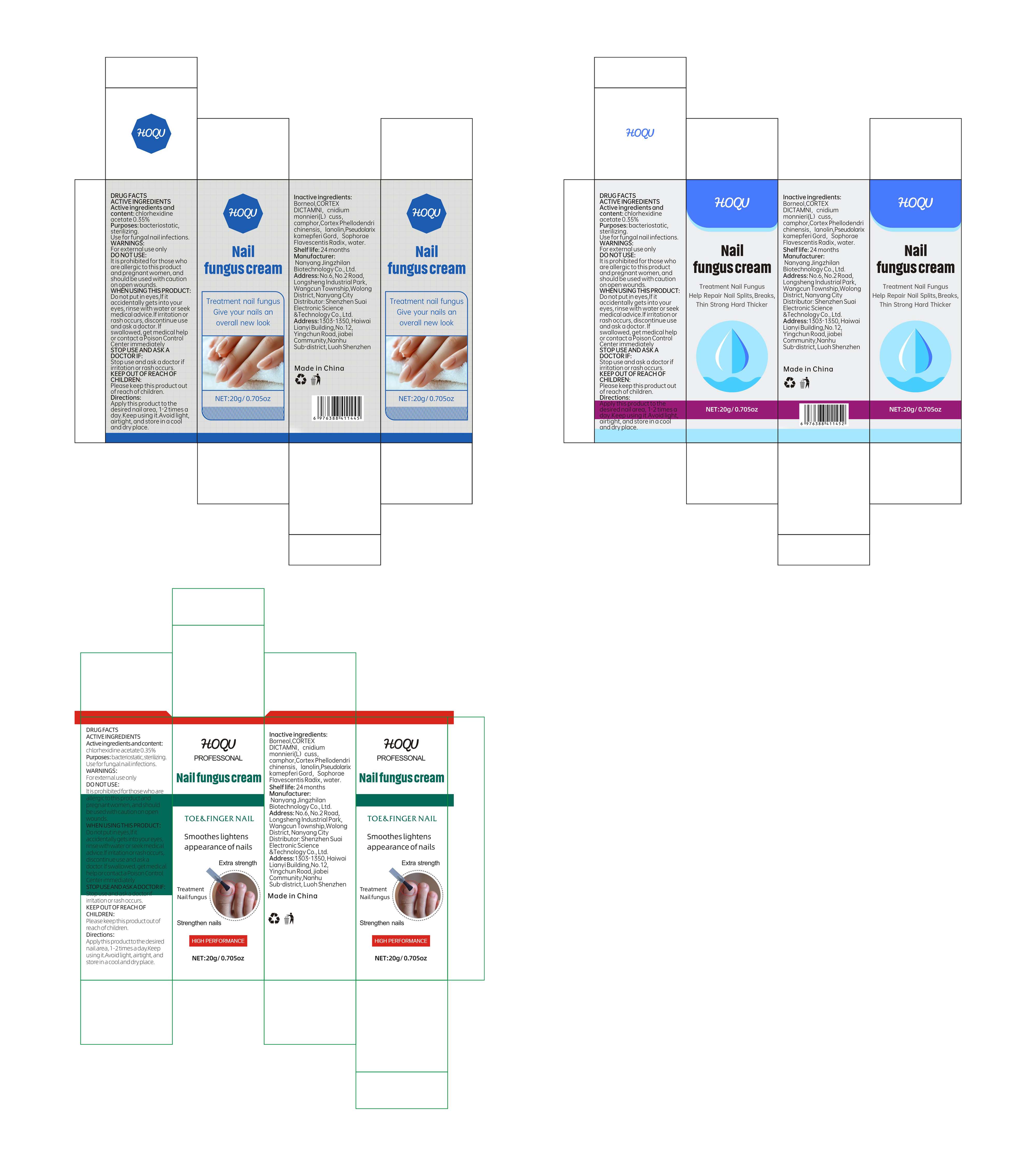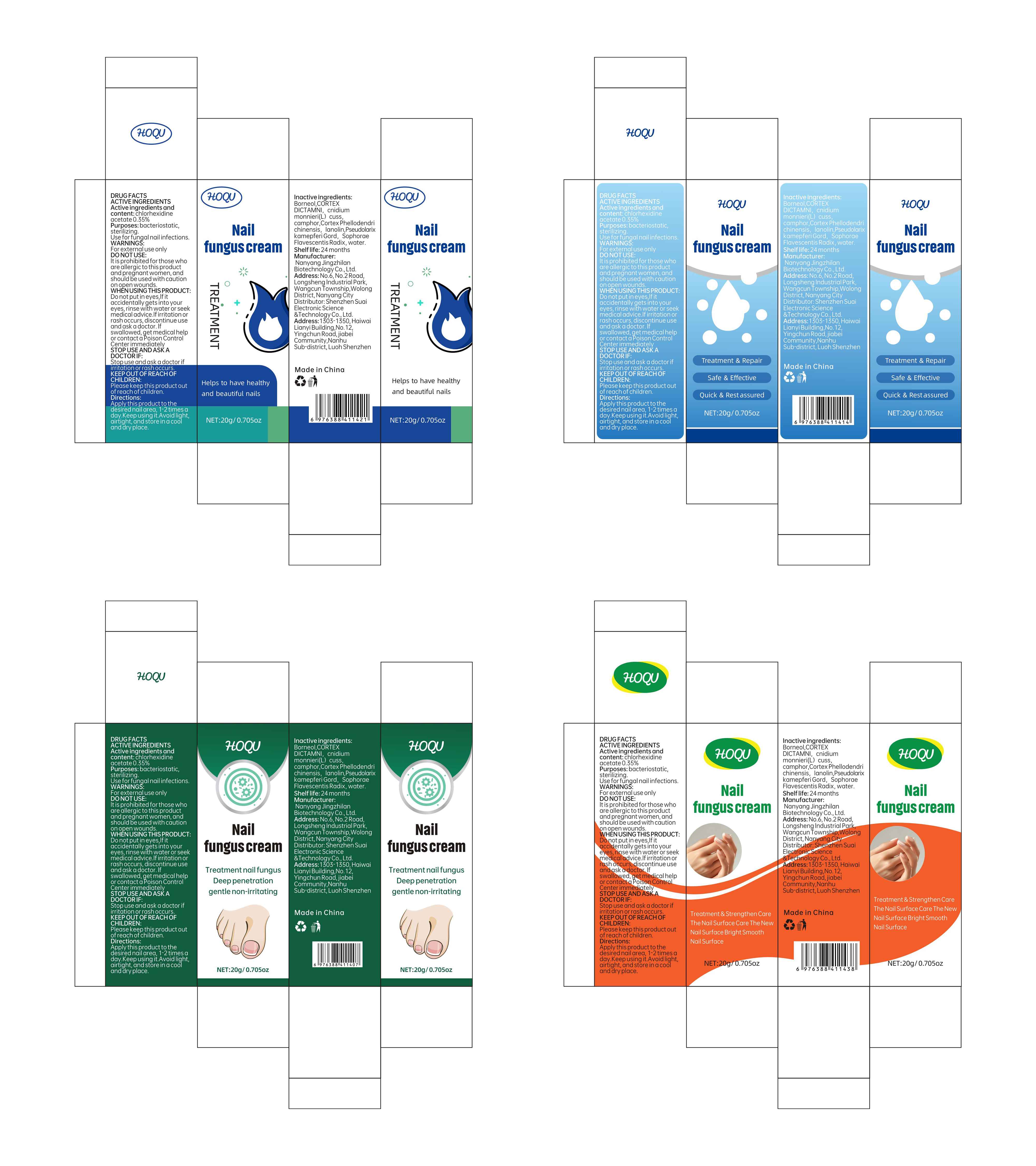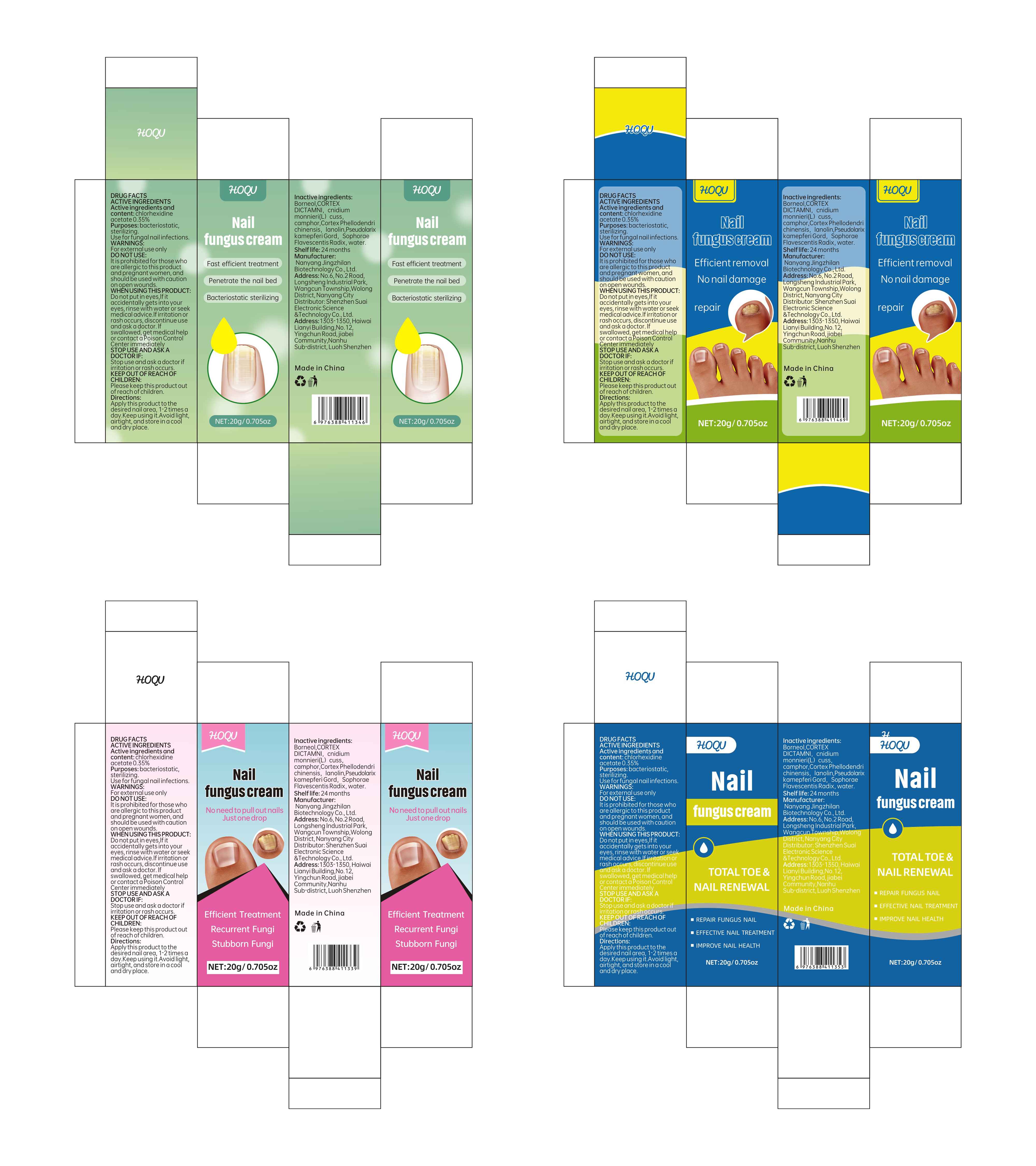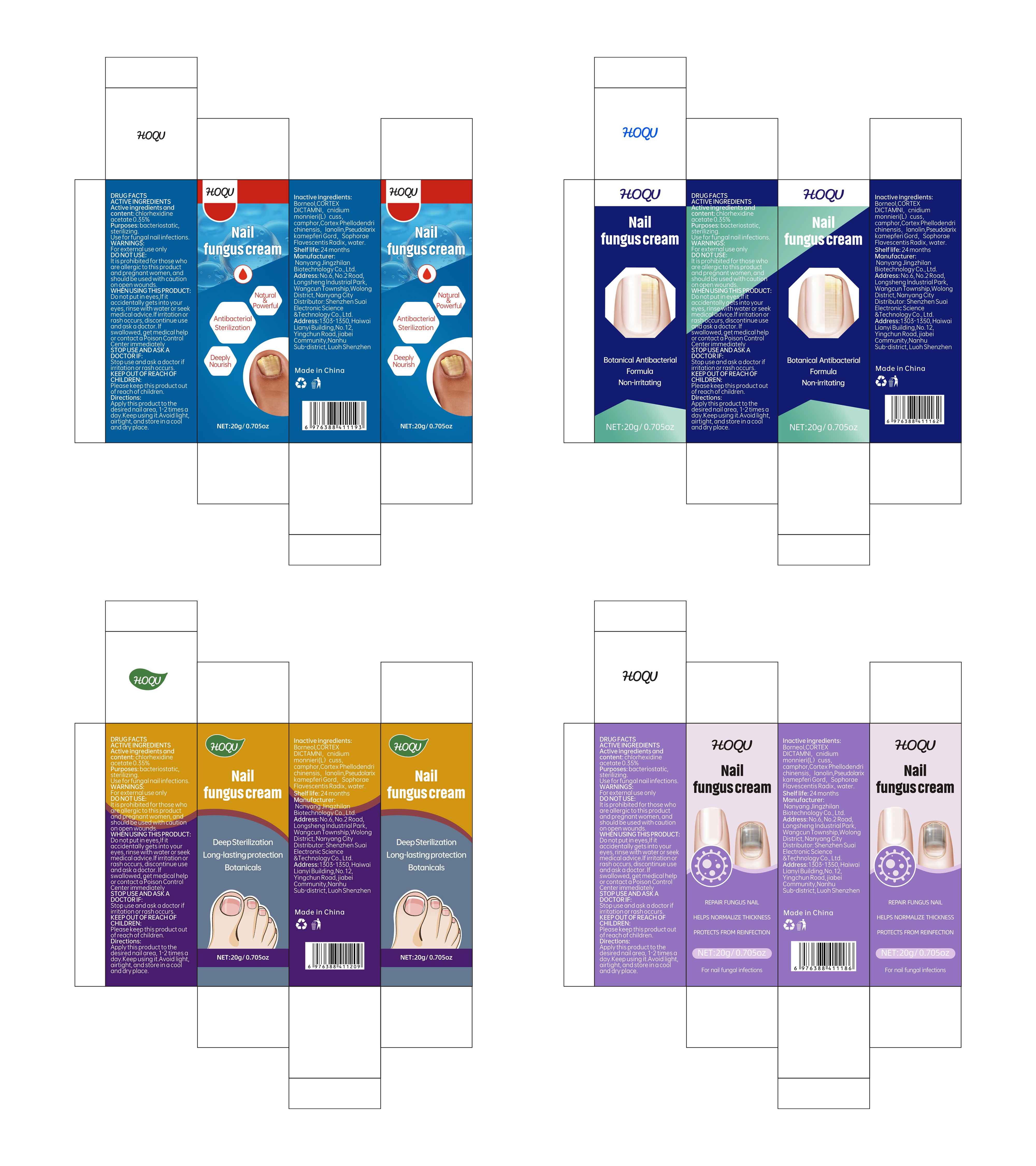 DRUG LABEL: HOQU Nail fungus cream
NDC: 84095-003 | Form: PASTE
Manufacturer: Shenzhen Suai Electronic Science & Technology Co., Ltd.
Category: otc | Type: HUMAN OTC DRUG LABEL
Date: 20240514

ACTIVE INGREDIENTS: CHLORHEXIDINE ACETATE 1 g/100 g
INACTIVE INGREDIENTS: DICTAMNUS DASYCARPUS ROOT; CAMPHORIC ACID, (-)-; QUERCUS SUBER BARK; WATER; PSEUDOLARIX AMABILIS BARK; BORNEOL; CNIDIUM MONNIERI FRUIT; LANOLIN; SOPHORA FLAVESCENS ROOT

84095-003 Update Manufacturer

Active Ingredient

chlorhexidine acetate 0.35%

Purpose

bacteriostatic, sterilizing

Use

Use for fungal nail infections

Warnings

For external use only

Do not use

lt is prohibited for those who are allergic to this product and pregnant women, and should be used with caution on open wounds.

When Using

Do not put in eyes,lf it accidentally gets into your eyes, rinse with water or seek medical advice.lf irritation or rash occurs, discontinue use and ask a doctor. lf swallowed, get medical help or contact a Poison Control Center immediately

Stop Use

Stop use and ask a doctor if irritation or rash occurs

Ask Doctor

Stop use and ask a doctor if irritation or rash occurs.

Keep Oot Of Reach Of Children

Please keep this product out of reach of children

Directions

Apply this product to the desired nail area, 1-2 times a day.Keep using it.Avoid light, airtight, and store in a cool and dry place.

Inactive ingredients

Borneol,CORTEX DICTAMNI, cnidium monnieri(L)cuss, camphor, Cortex Phellodendri chinensis, lanolin, Pseudolarix kamepferi Gord, Sophorae Flavescentis Radix, water.